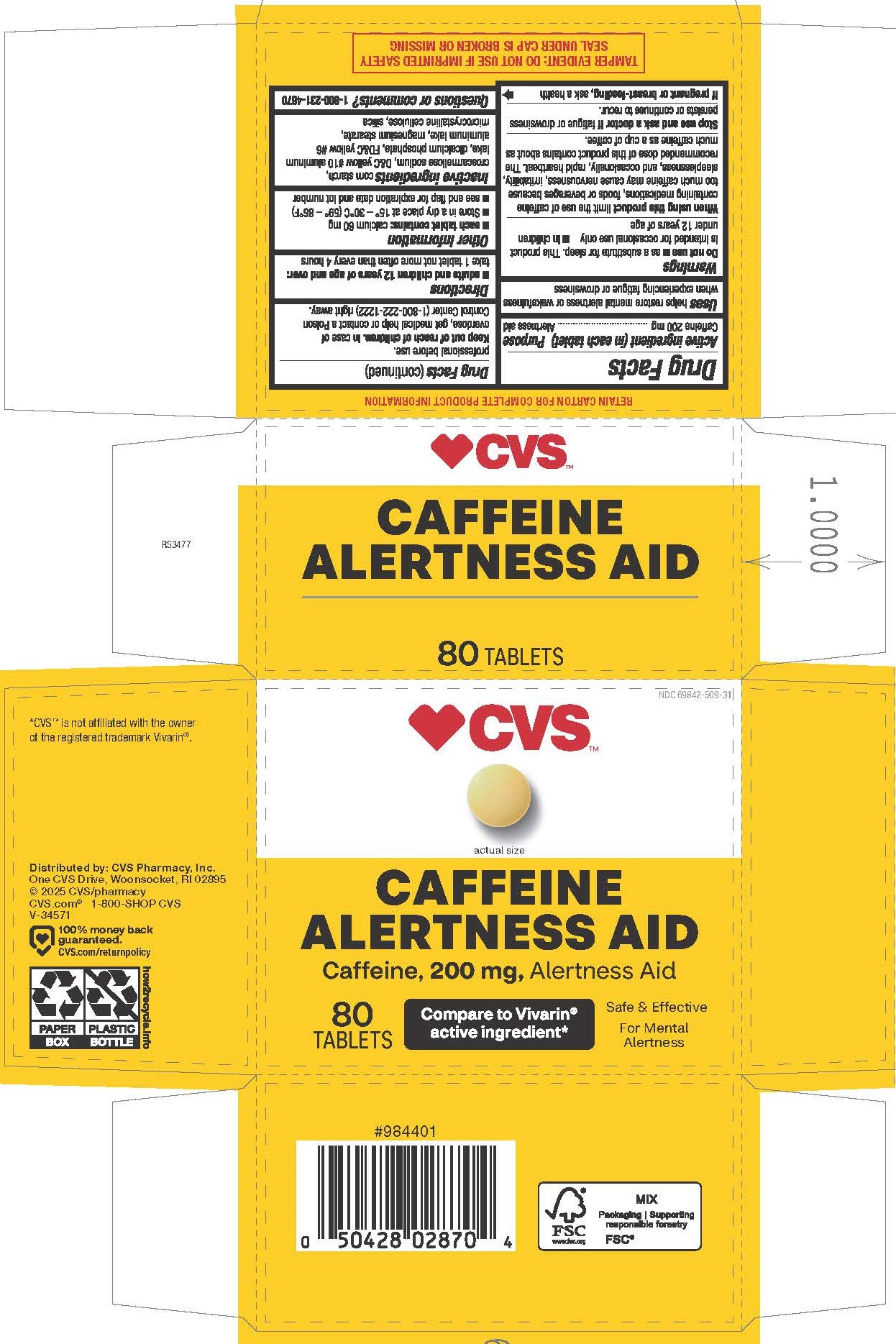 DRUG LABEL: Caffeine
NDC: 69842-509 | Form: TABLET
Manufacturer: CVS Pharmacy, Inc.
Category: otc | Type: HUMAN OTC DRUG LABEL
Date: 20260224

ACTIVE INGREDIENTS: CAFFEINE 200 mg/1 1
INACTIVE INGREDIENTS: D&C YELLOW NO. 10; SILICON DIOXIDE; DIBASIC CALCIUM PHOSPHATE DIHYDRATE; FD&C YELLOW NO. 6; STARCH, PREGELATINIZED CORN; MICROCRYSTALLINE CELLULOSE; MAGNESIUM STEARATE; CROSCARMELLOSE SODIUM

5009-CVS

Drug Facts

Active ingredient (in each tablet)

Caffeine 200 mg

Purpose

Alertness aid

Uses

helps restore mental alertness or wakefulness when experiencing fatigue or drowsiness

Warnings

Do not use

■ as a substitute for sleep. This product is intended for occasional use only ■ in children under 12 years of age

When using this product

limit the use of caffeine containing medications, foods or beverages because too much caffeine may cause nervousness, irritability, sleeplessness, and occasionally, rapid heartbeat. The recommended dose of this product contains about as much caffeine as a cup of coffee.

Stop use and ask a doctor if

fatigue or drowsiness persists or continues to recur.

If pregnant or breast-feeding,

ask a health professional before use.

Keep out of reach of children.

OVERDOSAGE

In case of overdose, get medical help or contact a Poison Control Center (1-800-222-1222) right away.

Directions

■ adults and children 12 years of age and over: take 1 tablet not more often than every 4 hours

Other information

- each tablet contains: calcium 60 mg
- Store in a dry place at 15° – 30°C (59° – 86°F)
- see end flap for expiration date and lot number

Inactive ingredients

corn starch, croscarmellose sodium, D&C yellow #10 aluminum lake, dicalcium phosphate, FD&C yellow #6 aluminum lake, magnesium stearate, microcrystalline cellulose, silica

Questions or comments?

1-800-231-4670

TAMPER EVIDENT: DO NOT USE IF IMPRINTED SAFETY SEAL UNDER CAP IS BROKEN OR MISSING

*CVS™ is not affiliated with the owner of the registered trademark Vivarin®.

Distributed by: CVS Pharmacy, Inc.

One CVS Drive, Woonsocket, RI 02895
© 2025 CVS/pharmacy
CVS.com® 1-800-SHOP CVS

V-34571

PACKAGE LABEL

CVS™

NDC 69842-509-31

CAFFEINE

ALERTNESS AID

Caffeine, 200 mg, Alertness Aid

80 TABLETS

Compare to Vivarin® active ingredient*

Safe & Effective

For Mental Alertness